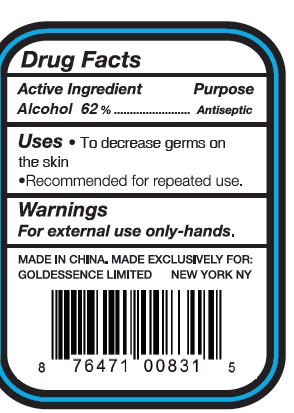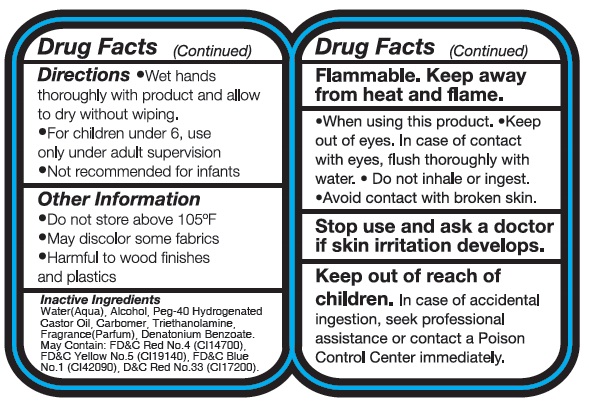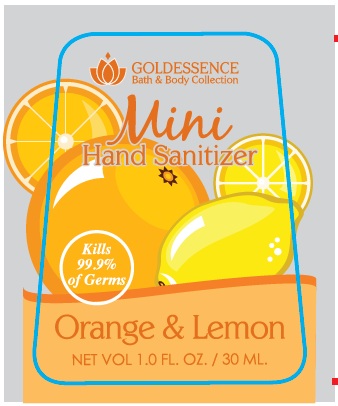 DRUG LABEL: MINI HAND SANITIZER - ORANGE AND LEMON
NDC: 51201-100 | Form: LIQUID
Manufacturer: Goldessence, Limited
Category: otc | Type: HUMAN OTC DRUG LABEL
Date: 20100728

ACTIVE INGREDIENTS: ALCOHOL 62 mL/100 mL
INACTIVE INGREDIENTS: WATER; TROLAMINE; DENATONIUM BENZOATE

MINI HAND SANITIZER ORANGE AND LEMON

Drug Facts

Active Ingredients.........................purpose

Alcohol 62%.....................................antiseptic

Uses:

To decrease germs on the skin

recommended for repeated use.

WARNINGS

Warning. For external use only-hands

MADE IN CHINA. MADE EXCLUSIVELY FOR GOLDESSENCE LIMITED NEW YORK NY

Directions

Wet hands thoroughly with product and allow to dry with out wiping

For children under 6, use only under adult supervision

not recommended for infants.

Other Information

Do not store above 105oC

May discolor some fabrics

Harmful to wood finishes and plastics

Inactive Ingredients

Water (aqua), Alcohol, Peg-40 Hydrogenated Castor Oil, Carbomer, Triethanolamine, Fragrance (parfum) Denatonium Benzoate. May contain FD and C Red No4 (CI14700), FD and C yellow No 5 (CI 19140), FD and C blue no1(CI42090), Dand C Red No 33 (CI17200)

Flammable. Keep away from heat and flame

When using this product. keep out of eyes. In case of contact with eyes, flush thoroughly with water,

do not inhale or ingest. avoid contact with broken skin.

Stop use and ask a doctor if skin irritation develops.

keep out of reach of children. In case of accidental ingestion, seek professional assistance or contact a poison control center immediately.

PACKAGE LABEL

goldessence bath and body collection

Mini Hand Sanitizer

Orange and Lemon

Kills 99.5%of germs

Net Vol 1.0 fl. oz / 30ml